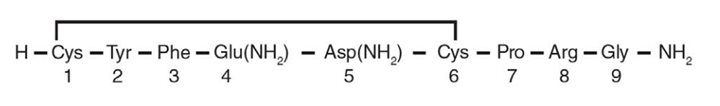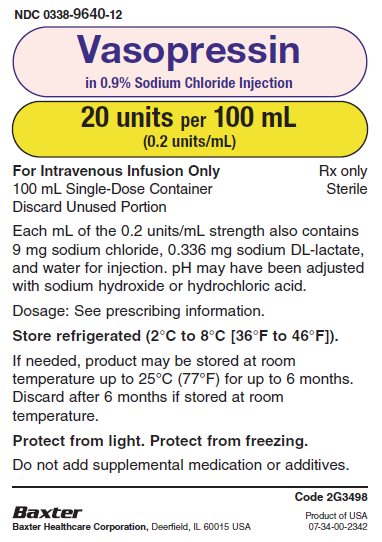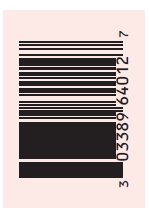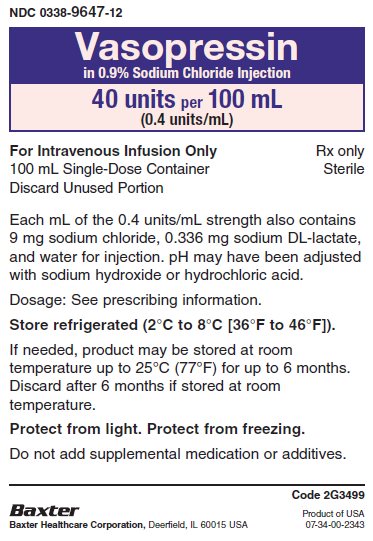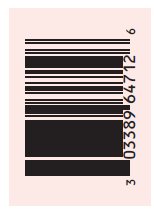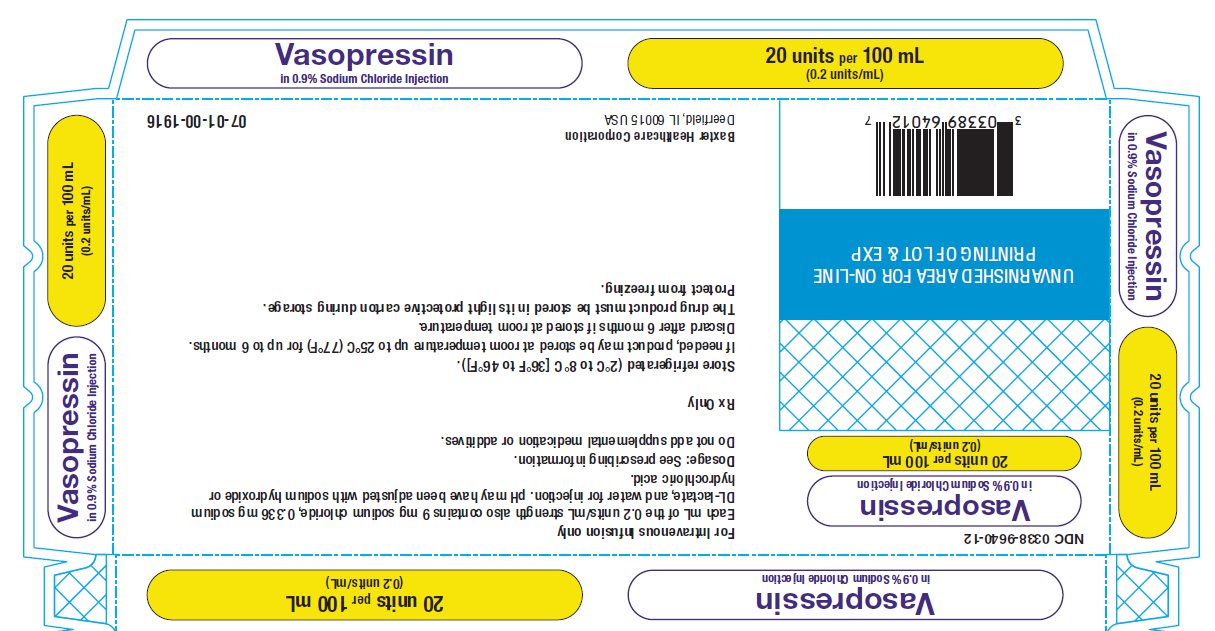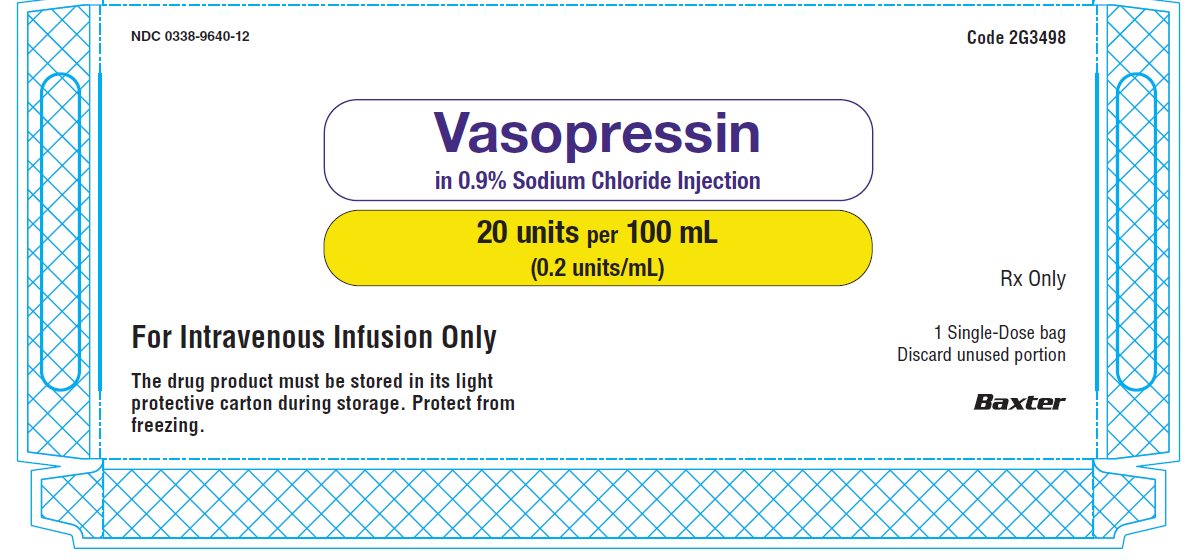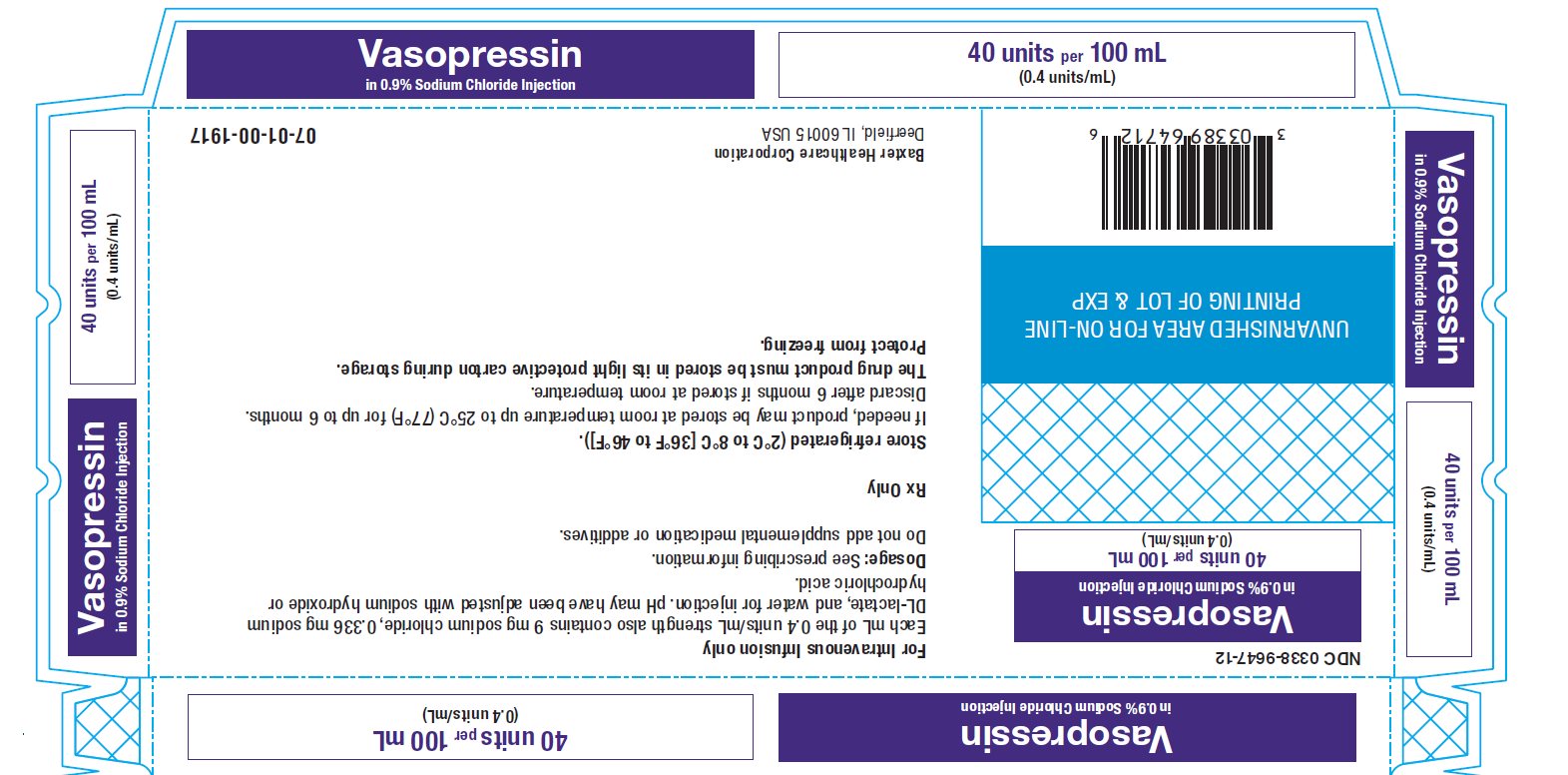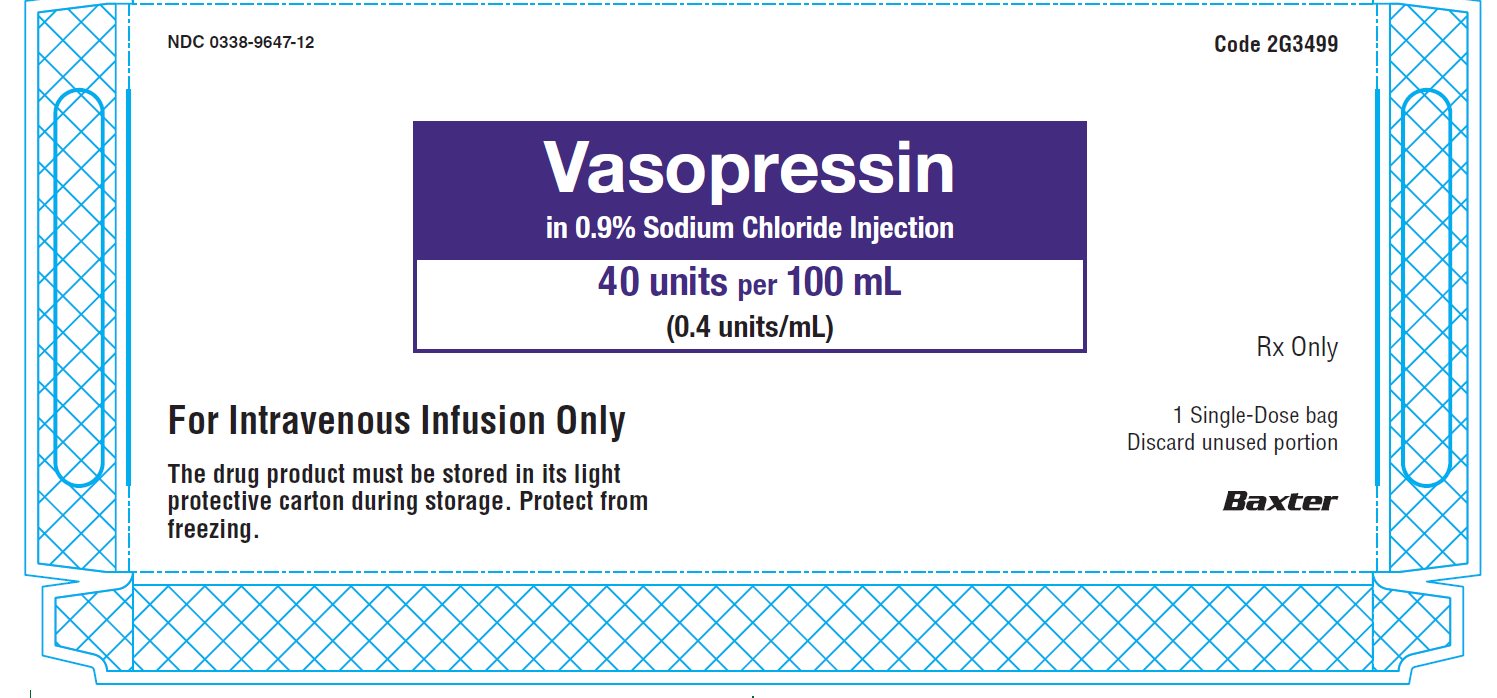 DRUG LABEL: Vasopressin in 0.9% Sodium Chloride
NDC: 0338-9640 | Form: INJECTION
Manufacturer: Baxter Healthcare Corporation
Category: prescription | Type: HUMAN PRESCRIPTION DRUG LABEL
Date: 20250221

ACTIVE INGREDIENTS: VASOPRESSIN 20 [USP'U]/100 mL
INACTIVE INGREDIENTS: SODIUM CHLORIDE 900 mg/100 mL; SODIUM LACTATE 33.6 mg/100 mL; WATER

HIGHLIGHTS OF PRESCRIBING INFORMATION

These highlights do not include all the information needed to use VASOPRESSIN IN SODIUM CHLORIDE INJECTION safely and effectively. See full prescribing information for VASOPRESSIN IN SODIUM CHLORIDE INJECTION.
VASOPRESSIN IN SODIUM CHLORIDE INJECTION, for intravenous use
Initial U.S. Approval: 2014

1 INDICATIONS AND USAGE

Vasopressin in Sodium Chloride Injection is indicated to increase blood pressure in adults with vasodilatory shock who remain hypotensive despite fluids and catecholamines. (1)

2 DOSAGE AND ADMINISTRATION

- Post-cardiotomy shock: 0.03 units/minute to 0.1 units/minute by intravenous infusion. (2.1)
- Septic shock: 0.01 units/minute to 0.07 units/minute by intravenous infusion. (2.1)

3 DOSAGE FORMS AND STRENGTHS

Injection: 100-mL single dose, ready-to-use containers with (3)

- 20 units vasopressin (0.2 units/mL) in 0.9% sodium chloride.
- 40 units vasopressin (0.4 units/mL) in 0.9% sodium chloride.

4 CONTRAINDICATIONS

- Vasopressin in Sodium Chloride Injection is contraindicated in patients with known allergy or hypersensitivity to 8-L-arginine vasopressin. (4)

5 WARNINGS AND PRECAUTIONS

- Can worsen cardiac function (5.1)
- Reversible diabetes insipidus (5.2)

6 ADVERSE REACTIONS

The most common adverse reactions include decreased cardiac output, bradycardia, tachyarrhythmias, hyponatremia and ischemia (coronary, mesenteric, skin, digital). (6)

To report SUSPECTED ADVERSE REACTIONS, contact Baxter Healthcare at 1-866-888-2472 or FDA at 1-800-FDA-1088 or www.fda.gov/medwatch.

7 DRUG INTERACTIONS

- Pressor effects of catecholamines and Vasopressin in Sodium Chloride Injection are expected to be additive. (7.1)
- Indomethacin may prolong effects of Vasopressin in Sodium Chloride Injection. (7.2)
- Co-administration of ganglionic blockers or drugs causing SIADH (syndrome of inappropriate antiduretic hormone secretion) may increase the pressor response. (7.3, 7.4)
- Co-administration of drugs causing diabetes insipidus may decrease the pressor response. (7.5)

8 USE IN SPECIFIC POPULATIONS

- Pregnancy: May induce tonic uterine contractions. (8.1)
- Pediatric Use: Safety and effectiveness have not been established. (8.4)
- Geriatric Use: No safety issues have not been identified in older patients. (8.5)

FULL PRESCRIBING INFORMATION

1 INDICATIONS AND USAGE

Vasopressin in Sodium Chloride Injection is indicated to increase blood pressure in adults with vasodilatory shock who remain hypotensive despite fluids and catecholamines.

2 DOSAGE AND ADMINISTRATION

2.1 Administration

This product does not require dilution prior to administration.

In general, titrate to the lowest dose compatible with a clinically acceptable response.

The recommended starting dose is:

Post-cardiotomy shock: 0.03 units/minute by intravenous infusion

Septic Shock: 0.01 units/minute by intravenous infusion

Titrate up by 0.005 units/minute at 10- to 15-minute intervals until the target blood pressure is reached. There are limited data for doses above 0.1 units/minute for post-cardiotomy shock and 0.07 units/minute for septic shock. Adverse reactions are expected to increase with higher doses.

After target blood pressure has been maintained for 8 hours without the use of catecholamines, taper vasopressin injection by 0.005 units/minute every hour as tolerated to maintain target blood pressure.

Inspect visually for any particulate matter and discoloration prior to administration.

Discard Unused Portion

Do not add supplemental medication or additive

3 DOSAGE FORMS AND STRENGTHS

Injection: a clear, practically colorless solution for intravenous infusion, supplied in 100-mL single dose ready-to-use containers as:

- 20 units vasopressin (0.2 units/mL) in 0.9% sodium chloride
- 40 units vasopressin (0.4 units/mL) in 0.9% sodium chloride

4 CONTRAINDICATIONS

Vasopressin in Sodium Chloride Injection is contraindicated in patients with a known allergy or hypersensitivity to 8-L-arginine vasopressin.

5 WARNINGS AND PRECAUTIONS

5.1 Worsening Cardiac Function

A decrease in cardiac index may be observed with the use of vasopressin.

5.2 Reversible Diabetes Insipidus

Patients may experience reversible diabetes insipidus, manifested by the development of polyuria, a dilute urine, and hypernatremia, after cessation of treatment with vasopressin. Monitor serum electrolytes, fluid status and urine output after vasopressin discontinuation. Some patients may require readministration of vasopressin or administration of desmopressin to correct fluid and electrolyte shifts.

6 ADVERSE REACTIONS

The following adverse reactions associated with the use of vasopressin were identified in the literature. Because these reactions are reported voluntarily from a population of uncertain size, it is not possible to estimate reliably their frequency or establish a causal relationship to drug exposure.

Bleeding/lymphatic system disorders: Hemorrhagic shock, decreased platelets, intractable bleeding

Cardiac disorders: Right heart failure, atrial fibrillation, bradycardia, myocardial ischemia

Gastrointestinal disorders: Mesenteric ischemia

Hepatobiliary: Increased bilirubin levels

Renal/urinary disorders: Acute renal insufficiency

Vascular disorders: Distal limb ischemia

Metabolic: Hyponatremia

Skin: Ischemic lesions

Postmarketing Experience

Reversible diabetes insipidus [see Warnings and Precautions (5.2)]

7 DRUG INTERACTIONS

7.1 Catecholamines

Use with catecholamines is expected to result in an additive effect on mean arterial blood pressure and other hemodynamic parameters. Hemodynamic monitoring is recommended; adjust the dose of vasopressin as needed.

7.2 Indomethacin

Use with indomethacin may prolong the effect of Vasopressin in Sodium Chloride Injection on cardiac index and systemic vascular resistance. Hemodynamic monitoring is recommended; adjust the dose of vasopressin as needed [see Clinical Pharmacology (12.3)].

7.3 Ganglionic Blocking Agents

Use with ganglionic blocking agents may increase the effect of Vasopressin in Sodium Chloride Injection on mean arterial blood pressure. Hemodynamic monitoring is recommended; adjust the dose of vasopressin as needed [see Clinical Pharmacology (12.3)].

7.4 Drugs Suspected of Causing SIADH

Use with drugs suspected of causing SIADH (e.g., SSRIs, tricyclic antidepressants, haloperidol, chlorpropamide, enalapril, methyldopa, pentamidine, vincristine, cyclophosphamide, ifosfamide, felbamate) may increase the pressor effect in addition to the antidiuretic effect of Vasopressin in Sodium Chloride Injection. Hemodynamic monitoring is recommended; adjust the dose of vasopressin as needed.

7.5 Drugs Suspected of Causing Diabetes Insipidus

Use with drugs suspected of causing diabetes insipidus (e.g., demeclocycline, lithium, foscarnet, clozapine) may decrease the pressor effect in addition to the antidiuretic effect of Vasopressin in Sodium Chloride Injection. Hemodynamic monitoring is recommended; adjust the dose of vasopressin as needed.

8 USE IN SPECIFIC POPULATIONS

8.1 Pregnancy

Risk Summary

There are no available data on Vasopressin in Sodium Chloride Injection use in pregnant women to inform a drug associated risk of major birth defects, miscarriage, or adverse maternal or fetal outcomes. Animal reproduction studies have not been conducted.

Clinical Considerations

Dose Adjustments During Pregnancy and the Postpartum Period: Because of increased clearance of vasopressin in the second and third trimester, the dose of Vasopressin in Sodium Chloride Injection may need to be increased [see Dosage and Administration (2.1) and Clinical Pharmacology (12.3)].
Maternal Adverse Reactions: Vasopressin in Sodium Chloride Injection may produce tonic uterine contractions that could threaten the continuation of pregnancy.

8.2 Lactation

There are no data on the presence of vasopressin injection in either human or animal milk, the effects on the breastfed infant, or the effects on milk production.

8.4 Pediatric Use

Safety and effectiveness of Vasopressin in Sodium Chloride Injection in pediatric patients with vasodilatory shock have not been established.

8.5 Geriatric Use

Clinical studies of vasopressin did not include sufficient numbers of subjects aged 65 and over to determine whether they respond differently from younger subjects. Other reported clinical experience has not identified differences in responses between the elderly and younger patients. In general, dose selection for an elderly patient should be cautious, usually starting at the low end of the dosing range, reflecting the greater frequency of decreased hepatic, renal, or cardiac function, and of concomitant disease or other drug therapy [see Warnings and Precautions (5), Adverse Reactions (6), and Clinical Pharmacology (12.3)].

10 OVERDOSAGE

Overdosage with Vasopressin in Sodium Chloride Injection can be expected to manifest as consequences of vasoconstriction of various vascular beds (peripheral, mesenteric, and coronary) and as hyponatremia. In addition, overdosage may lead less commonly to ventricular tachyarrhythmias (including Torsade de Pointes), rhabdomyolysis, and non-specific gastrointestinal symptoms.

Direct effects will resolve within minutes of withdrawal of treatment.

11 DESCRIPTION

Vasopressin in Sodium Chloride Injection contains vasopressin, a polypeptide hormone. The chemical name of vasopressin is Cyclo (1-6) L-Cysteinyl-L-Tyrosyl-L-Phenylalanyl-L-Glutaminyl-L-Asparaginyl-L-Cysteinyl-L-Prolyl-L-Arginyl-L-Glycinamide. It is a white to off-white amorphous powder, freely soluble in water. The structural formula is:

Molecular Formula: C46H65N15O12S2 Molecular Weight: 1084.23

Vasopressin in Sodium Chloride Injection is a sterile, aqueous solution of synthetic arginine vasopressin for intravenous administration. Each 100 mL contains 20 units (0.2 units/mL) or 40 units (0.4 units/mL) of vasopressin. Each 100mL also contains 900 mg Sodium Chloride, 33.6 mg Sodium DL-Lactate, and Water for Injection. pH may have been adjusted with sodium hydroxide and/or hydrochloric acid. It has a pH of 3.6 – 4.0.

12 CLINICAL PHARMACOLOGY

12.1 Mechanism of Action

Vasopressin causes vasoconstriction by binding to V1 receptors on vascular smooth muscle coupled to the Gq/11-phospholipase C-phosphatidyl-inositol-triphosphate pathway, resulting in the release of intracellular calcium. In addition, vasopressin stimulates antidiuresis via stimulation of V2 receptors which are coupled to adenyl cyclase.

12.2 Pharmacodynamics

At therapeutic doses exogenous vasopressin elicits a vasoconstrictive effect in most vascular beds including the splanchnic, renal and cutaneous circulation. In addition, vasopressin at pressor doses triggers contractions of smooth muscles in the gastrointestinal tract mediated by muscular V1-receptors and release of prolactin and ACTH via V3 receptors. At lower concentrations typical for the antidiuretic hormone vasopressin inhibits water diuresis via renal V2 receptors. In addition, vasopressin has been demonstrated to cause vasodilation in numerous vascular beds that are mediated by V2, V3, oxytocin and purinergic P2 receptors.

In patients with vasodilatory shock vasopressin in therapeutic doses increases systemic vascular resistance and mean arterial blood pressure and reduces the dose requirements for norepinephrine. Vasopressin tends to decrease heart rate and cardiac output. The pressor effect is proportional to the infusion rate of exogenous vasopressin. The pressor effect reaches its peak within 15 minutes. After stopping the infusion the pressor effect fades within 20 minutes. There is no evidence for tachyphylaxis or tolerance to the pressor effect of vasopressin in patients.

12.3 Pharmacokinetics

Vasopressin plasma concentrations increase linearly with increasing infusion rates from 10 to 200 μU/kg/min. Steady state plasma concentrations are achieved after 30 minutes of continuous intravenous infusion.

Distribution

Vasopressin does not appear to bind plasma protein. The volume of distribution is 140 mL/kg.

Elimination

At infusion rates used in vasodilatory shock (0.01 to 0.1 units/minute), the clearance of vasopressin is 9 to 25 mL/min/kg in patients with vasodilatory shock. The apparent t1/2 of vasopressin at these levels is ≤10 minutes.

Metabolism

Serine protease, carboxipeptidase and disulfide oxido-reductase cleave vasopressin at sites relevant for the pharmacological activity of the hormone. Thus, the generated metabolites are not expected to retain important pharmacological activity.

Excretion

Vasopressin is predominantly metabolized and only about 6% of the dose is excreted unchanged into urine.

Specific Populations

Pregnancy: Because of a spillover into blood of placental vasopressinase, the clearance of exogenous and endogenous vasopressin increases gradually over the course of a pregnancy. During the first trimester of pregnancy, the clearance is only slightly increased. However, by the third trimester the clearance of vasopressin is increased about 4-fold and at term up to 5-fold. After delivery, the clearance of vasopressin returns to pre-conception baseline within two weeks.

Drug Interaction Studies

Indomethacin more than doubles the time to offset for vasopressin’s effect on peripheral vascular resistance and cardiac output in healthy subjects [see Drug Interactions (7.2)].
The ganglionic blocking agent tetra-ethylammonium increases the pressor effect of vasopressin by 20% in healthy subjects [see Drug Interactions (7.3)].
Halothane, morphine, fentanyl, alfentanyl and sufentanyl do not impact exposure to endogenous vasopressin.

13 NONCLINICAL TOXICOLOGY

13.1 Carcinogenesis, Mutagenesis, Impairment of Fertility

No formal carcinogenicity or fertility studies with vasopressin have been conducted in animals. Vasopressin was found to be negative in the in vitro bacterial mutagenicity (Ames) test and the in vitro Chinese hamster ovary (CHO) cell chromosome aberration test. In mice, vasopressin has been reported to have an effect on function and fertilizing ability of spermatozoa.

13.2 Animal Toxicology and/or Pharmacology

No toxicology studies were conducted with vasopressin.

14 CLINICAL STUDIES

Increases in systolic and mean blood pressure following administration of vasopressin were observed in 7 studies in septic shock and 8 in post-cardiotomy vasodilatory shock.

16 HOW SUPPLIED/STORAGE AND HANDLING

Vasopressin in Sodium Chloride Injection is supplied as a clear, practically colorless solution for intravenous administration in single-dose 100 mL ready-to-use containers available as:

Product Code | Product Description | NDC Number
2G3498 | 20 units vasopressin (0.2 units/mL); Supplied as 12 bags per carton | 0338-9640-12
2G3499 | 40 units vasopressin (0.4 units/mL); Supplied as 12 bags per carton | 0338-9647-12

Store in the refrigerator (2°C to 8°C [36°F to 46°F]). Protect from freezing.

If needed, Vasopressin in Sodium Chloride Injection may be stored at room temperature up to 25°C (77°F) for up to 6 months. Discard after 6 months if stored at room temperature or until the expiration date printed on the carton and container label, whichever is earlier. Once stored at room temperature, do not place back in the refrigerator.

The drug product must be stored in its light protective carton during storage.

Manufactured by, Packed by, Distributed by:

Baxter Healthcare Corporation

Deerfield, IL 60015 USA

Printed in USA

07-19-06-884

Baxter and Galaxy are trademarks of Baxter International Inc.

PACKAGE/LABEL PRINCIPAL DISPLAY PANEL

Container Label

NDC 0338-9640-12

Vasopressin
in 0.9% Sodium Chloride Injection
20 units per 100 mL
(0.2 units/mL)

For Intravenous Infusion Only
100 mL Single-Dose Container
Discard Unused Portion

Rx only
Sterile

Each mL of the 0.2 units/mL strength also contains
9 mg sodium chloride, 0.336 mg sodium DL-lactate,
and water for injection. pH may have been adjusted
with sodium hydroxide or hydrochloric acid.

Dosage: See prescribing information.

Store refrigerated (2°C to 8°C [36°F to 46°F]).

If needed, product may be stored at room
temperature up to 25°C (77°F) for up to 6 months.
Discard after 6 months if stored at room
temperature.

Protect from light. Protect from freezing.

Do not add supplemental medication or additives.

Code 2G3498

Baxter Logo
Baxter Healthcare Corporation, Deerfield, IL 60015 USA

Product of USA
07-34-00-2342

BAR CODE
303389640127

Container Label

NDC 0338-9647-12

Vasopressin
in 0.9% Sodium Chloride Injection
40 units per 100 mL
(0.4 units/mL)

For Intravenous Infusion Only
100 mL Single-Dose Container
Discard Unused Portion

Rx only
Sterile

Each mL of the 0.4 units/mL strength also contains
9 mg sodium chloride, 0.336 mg sodium DL-lactate,
and water for injection. pH may have been adjusted
with sodium hydroxide or hydrochloric acid.

Dosage: See prescribing information.

Store refrigerated (2°C to 8°C [36°F to 46°F]).

If needed, product may be stored at room
temperature up to 25°C (77°F) for up to 6 months.
Discard after 6 months if stored at room
temperature.

Protect from light. Protect from freezing.

Do not add supplemental medication or additives.

Code 2G3499

Baxter Logo
Baxter Healthcare Corporation, Deerfield, IL 60015 USA

Product of USA
07-34-00-2343

BAR CODE
303389647126

Carton Label

Vasopressin
in 0.9% Sodium Chloride Injection

20 units per 100 mL
(0.2 units/mL)

Vasopressin
in 0.9% Sodium Chloride Injection

20 units per 100 mL
(0.2 units/mL)

NDC 0338-9640-12

Vasopressin
in 0.9% Sodium Chloride Injection
20 units per 100 mL
(0.2 units/mL)

UNVARNISHED AREA FOR ON-LINE
PRINTING OF LOT & EXP

Bar Code
303389640127

For Intravenous Infusion only
Each mL of the 0.2 units/mL strength also contains 9 mg sodium chloride, 0.336 mg sodium
DL-lactate, and water for injection. pH may have been adjusted with sodium hydroxide or
hydrochloric acid.
Dosage: See prescribing information.
Do not add supplemental medication or additives.

Rx only

Store refrigerated (2°C to 8°C [36°F to 46°F]).
If needed, product may be stored at room temperature up to 25°C (77°F) for up to 6 months.
Discard after 6 months if stored at room temperature.
The drug product must be stored in its light protective carton during storage.
Protect from freezing.

Baxter Healthcare Corporation
Deerfield, IL 60015 USA

07-01-00-1916

Vasopressin
in 0.9% Sodium Chloride Injection

20 units per 100 mL
(0.2 units/mL)

Vasopressin
in 0.9% Sodium Chloride Injection

20 units per 100 mL
(0.2 units/mL)

NDC 0338-9640-12

Vasopressin
in 0.9% Sodium Chloride Injection

20 units per 100 mL
(0.2 units/mL)

For Intravenous Infusion Only

The drug product must be stored in its light
protective carton during storage. Protect from
freezing.

Code 2G3498

Rx only

1 Single-Dose bag
Discard unused portion

Baxter logo

Carton Label

Vasopressin
in 0.9% Sodium Chloride Injection

40 units per 100 mL
(0.4 units/mL)

Vasopressin
in 0.9% Sodium Chloride Injection

40 units per 100 mL
(0.4 units/mL)

NDC 0338-9647-12

Vasopressin
in 0.9% Sodium Chloride Injection
40 units per 100 mL
(0.4 units/mL)

UNVARNISHED AREA FOR ON-LINE
PRINTING OF LOT & EXP

Bar Code
303389647126

For Intravenous Infusion only
Each mL of the 0.4 units/mL strength also contains 9 mg sodium chloride, 0.336 mg sodium
DL-lactate, and water for injection. pH may have been adjusted with sodium hydroxide or
hydrochloric acid.
Dosage: See prescribing information.
Do not add supplemental medication or additives.

Rx only

Store refrigerated (2°C to 8°C [36°F to 46°F]).
If needed, product may be stored at room temperature up to 25°C (77°F) for up to 6 months.
Discard after 6 months if stored at room temperature.
The drug product must be stored in its light protective carton during storage.
Protect from freezing.

Baxter Healthcare Corporation
Deerfield, IL 60015 USA

07-01-00-1917

Vasopressin
in 0.9% Sodium Chloride Injection

40 units per 100 mL
(0.4 units/mL)

Vasopressin
in 0.9% Sodium Chloride Injection

40 units per 100 mL
(0.4 units/mL)

NDC 0338-9647-12

Vasopressin
in 0.9% Sodium Chloride Injection

40 units per 100 mL
(0.4 units/mL)

For Intravenous Infusion Only

The drug product must be stored in its light
protective carton during storage. Protect from
freezing.

Code 2G3499

Rx only

1 Single-Dose bag
Discard unused portion

Baxter logo